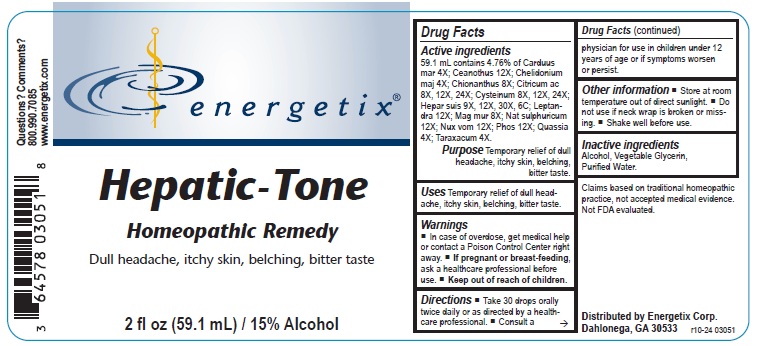 DRUG LABEL: Hepatic-Tone
NDC: 64578-0085 | Form: LIQUID
Manufacturer: Energetix Corporation
Category: homeopathic | Type: HUMAN OTC DRUG LABEL
Date: 20241120

ACTIVE INGREDIENTS: MILK THISTLE 4 [hp_X]/1 mL; CEANOTHUS AMERICANUS LEAF 12 [hp_X]/1 mL; CHELIDONIUM MAJUS 4 [hp_X]/1 mL; CHIONANTHUS VIRGINICUS BARK 8 [hp_X]/1 mL; ANHYDROUS CITRIC ACID 8 [hp_X]/1 mL; CYSTEINE 8 [hp_X]/1 mL; PORK LIVER 9 [hp_X]/1 mL; VERONICASTRUM VIRGINICUM ROOT 12 [hp_X]/1 mL; MAGNESIUM CHLORIDE 8 [hp_X]/1 mL; SODIUM SULFATE 12 [hp_X]/1 mL; STRYCHNOS NUX-VOMICA SEED 12 [hp_X]/1 mL; PHOSPHORUS 12 [hp_X]/1 mL; QUASSIA AMARA WOOD 4 [hp_X]/1 mL; TARAXACUM OFFICINALE 4 [hp_X]/1 mL
INACTIVE INGREDIENTS: WATER; GLYCERIN; ALCOHOL

Hepatic-Tone

Active ingredients

59.1 mL contains 4.76% of: Carduus mar 4X; Ceanothus 12X; Chelidonium maj 4X; Chionanthus 8X; Citricum ac 8X, 12X, 24X; Cysteinum 8X, 12X, 24X; Hepar suis 9X, 12X, 30X, 6C; Leptandra 12X; Mag mur 8X; Nat sulphuricum 12X; Nux vom 12X; Phos 12X; Quassia 4X; Taraxacum 4X.

Claims based on traditional homeopathic practice, not accepted medical evidence. Not FDA evaluated.

INDICATIONS AND USAGE

Uses Temporary relief of dull headache, itchy skin, belching, bitter taste.

Warnings

- In case of overdose, get medical help or contact a Poison Control Center right away.

- If pregnant or breast feeding,ask a health professional before use.

- Keep out of reach of children.

Directions

- Take 30 drops orally twice daily or as directed by a healthcare professional.
- Consult a physician for use in children under 12 years of age or if symptoms worsen or persist.

Other information

- Store at room temperature out of direct sunlight,
- Do not use if neck wrap is broken or missing.
- Shake well before use.

Inactive ingredients Alcohol, Vegetable Glycerin, Purified Water.

QUESTIONS

Distributed by Energetix Corp.

Dahlonega, GA 30533

Questions? Comments?

800.990.7085

www.energetix.com

PACKAGE LABEL

energetix

Hepatic - Tone

Homeopathic Remedy

Dull headache, itchy skin, belching, bitter taste

2 fl oz (59.1 mL) / 15% Alcohol

PURPOSE

Purpose Temporary relief of dull headache, itchy skin, belching, bitter taste.